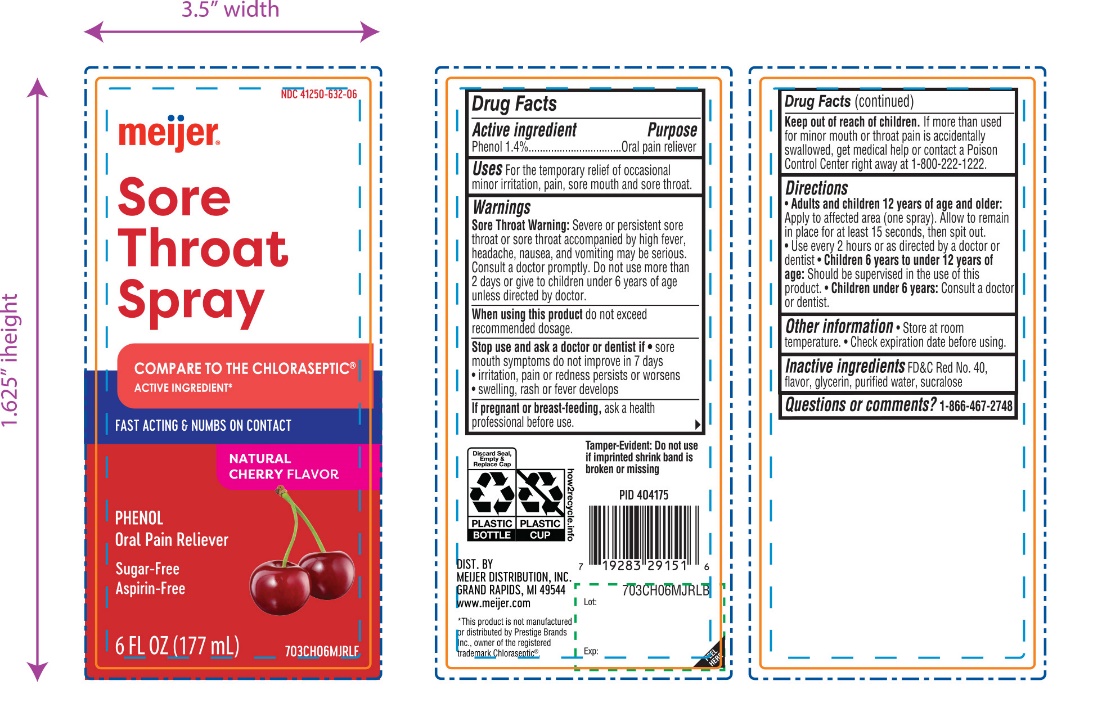 DRUG LABEL: Meijer Sore Throat
NDC: 41250-632 | Form: SPRAY
Manufacturer: MEIJER DISTRIBUTION INC.
Category: otc | Type: HUMAN OTC DRUG LABEL
Date: 20251024

ACTIVE INGREDIENTS: PHENOL 1.4 g/100 mL
INACTIVE INGREDIENTS: FD&C RED NO. 40; GLYCERIN; WATER; SUCRALOSE

Meijer Sore Throat Spray Drug Facts

Active Ingredient(s)

Phenol 1.4%

Purpose

Oral pain reliever

Use(s)

For the temporary relief of occasional minor irritation, pain, sore mouth and sore throat.

Warnings

Sore Throat Warning:Severe or persistent sore throat or sore throat that accompanied by high fever, headache, nausea, and vomiting may be serious. Consult a doctor promptly. Do not use more than 2 days or give to children under 6 years of age unless directed by doctor.

When using this product

do not exceed recommended dosage.

Stop use and ask a doctor if

- sore mouth symptoms do not improve in 7 days
- irritation, pain or redness persists or worsens
- swelling, rash or fever develops

If pregnant or breast feeding

ask a doctor before use.

Keep out of reach of children

If more than used for minor mouth or throat pain is accidentally swallowed, get medical help or contact a Poison Control Center right away. (1-800-222-1222).

Directions

- Adults and children 6 years of age and older:
  Apply to the affected area (one spray). Allow to remain in place for at least 15 seconds, and then spit out.
- Use every 2 hours or as directed by a doctor or dentist.
- Children 6 years to under 12 years of ageshould be supervised in the use of this product.
- Children under 6 years: Consult a doctor or dentist.

Other Information

- Store at room temperature
- Check expiration date before using.

Inactive Ingredients

FD&C Red No. 40, flavor, glycerin, purified water, sucralose

Questions or comments?

1-866-467-2748

Principal Display Panel

*Compare to Chloraseptic®active ingredient*

NDC# 41250-632-06

SORE THROAT SPRAY

Phenol/Oral Pain Reliever

Sugar-free

Aspirin-free

Alcohol-free

Natural Cherry Flavor

6 FL OZ (177 mL)

Tamper-Evident: Do not use if imprinted shrink band is broken or missing

DISTRIBUTED BY: MEIJER DISTRIBUTION, INC.

GRAND RAPIDS, MI 49544

www.meijer.com

*This product is not manufactured or distributed by Prestige Brands Inc., owner of the registered trademark Chloraseptic®.